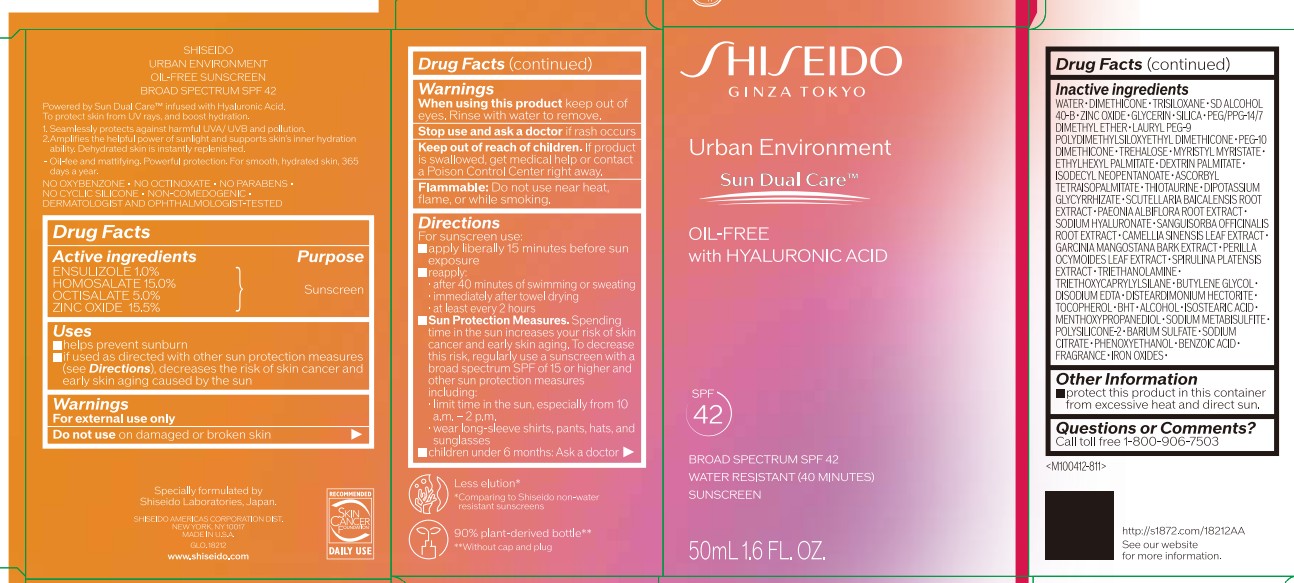 DRUG LABEL: SHISEIDO URBAN ENVIRONMENT
NDC: 58411-952 | Form: EMULSION
Manufacturer: Shiseido Americas Corporation
Category: otc | Type: HUMAN OTC DRUG LABEL
Date: 20251216

ACTIVE INGREDIENTS: ENSULIZOLE 0.6 g/50 mL; HOMOSALATE 9 g/50 mL; OCTISALATE 3 g/50 mL; ZINC OXIDE 9.3 g/50 mL
INACTIVE INGREDIENTS: WATER; DIMETHICONE; TRISILOXANE; ALCOHOL; GLYCERIN; SILICA; PEG/PPG-14/7 DIMETHYL ETHER; LAURYL PEG-9 POLYDIMETHYLSILOXYETHYL DIMETHICONE; PEG-10 DIMETHICONE (200 CST); TREHALOSE; MYRISTYL MYRISTATE; ETHYLHEXYL PALMITATE; DEXTRIN PALMITATE (CORN; 20000 MW); ISODECYL NEOPENTANOATE; ASCORBYL TETRAISOPALMITATE; THIOTAURINE; DIPOTASSIUM GLYCYRRHIZATE; SCUTELLARIA BAICALENSIS ROOT; PAEONIA ALBIFLORA FLOWER; SODIUM HYALURONATE; SANGUISORBA OFFICINALIS ROOT; CAMELLIA SINENSIS LEAF; GARCINIA MANGOSTANA BARK; PERILLA OCYMOIDES SEED OIL; SPIRULINA PLATENSIS; TRIETHANOLAMINE; TRIETHOXYCAPRYLYLSILANE; BUTYLENE GLYCOL; EDETATE DISODIUM; DISTEARDIMONIUM HECTORITE; TOCOPHEROL; BHT; ISOSTEARIC ACID; MENTHOXYPROPANEDIOL; SODIUM METABISULFITE; BARIUM SULFATE; SODIUM CITRATE; PHENOXYETHANOL; BENZOIC ACID; FERRIC OXIDE RED

SHISEIDO URBAN ENVIRONMENT

Drug Facts

Active ingredients | Purpose
Ensulizole 1.0% | Sunscreen
Homosalate 15.0% | Sunscreen
Octisalate 5.0% | Sunscreen
Zinc Oxide 15.5% | Sunscreen

Uses

- help prevent sunburn
- if used as directed with other sun protection measures (see Directions), decreases the risk of skin cancer and early skin aging caused by the sun

Warnings

For external use only

Do not use on damaged or broken skin

When using this product keep out of eyes. Rinse with water to remove.

Stop use and ask a doctor if rash occurs

Keep out of reach of children. If product is swallowed, get medical help or contact a Poison Control Center right away.

WARNINGS AND PRECAUTIONS

Flammable: Do not use near heat, flame, or while smoking

Directions

For sunscreen use:

- apply liberally 15 minutes before sun exposure
- reapply:

• after 40 minutes of swimming or sweating

• immediately after towel drying

• at least every 2 hours

- Sun Protection Measures. Spending time in the sun increases your risk of skin cancer and early skin aging. To decrease this risk, regularly use a sunscreen with a broad spectrum SPF of 15 or higher and other sun protection measures including:

• limit time in the sun, especially from 10 a.m. - 2 p.m.

• wear long-sleeve shirts, pants, hats, and sunglasses

• children under 6 months: Ask a doctor

INACTIVE INGREDIENT

WATER･DIMETHICONE･TRISILOXANE･SD ALCOHOL 40-B･ZINC OXIDE･GLYCERIN･SILICA･PEG/PPG-14/7 DIMETHYL ETHER･LAURYL PEG-9 POLYDIMETHYLSILOXYETHYL DIMETHICONE･PEG-10 DIMETHICONE･TREHALOSE･MYRISTYL MYRISTATE･ETHYLHEXYL PALMITATE･DEXTRIN PALMITATE･ISODECYL NEOPENTANOATE･ASCORBYL TETRAISOPALMITATE･THIOTAURINE･DIPOTASSIUM GLYCYRRHIZATE･SCUTELLARIA BAICALENSIS ROOT EXTRACT･PAEONIA ALBIFLORA ROOT EXTRACT･SODIUM HYALURONATE･SANGUISORBA OFFICINALIS ROOT EXTRACT･CAMELLIA SINENSIS LEAF EXTRACT･GARCINIA MANGOSTANA BARK EXTRACT･PERILLA OCYMOIDES LEAF EXTRACT･SPIRULINA PLATENSIS EXTRACT･TRIETHANOLAMINE･TRIETHOXYCAPRYLYLSILANE･BUTYLENE GLYCOL･DISODIUM EDTA･DISTEARDIMONIUM HECTORITE･TOCOPHEROL･BHT･ALCOHOL･ISOSTEARIC ACID･MENTHOXYPROPANEDIOL･SODIUM METABISULFITE･POLYSILICONE-2･BARIUM SULFATE･SODIUM CITRATE･PHENOXYETHANOL･BENZOIC ACID･FRAGRANCE･IRON OXIDES･

Other information

- protect this product in this container from excessive heat and direct sunlight

Questions or Comments?

Call toll free 1-800-906-7503

PACKAGE LABEL

SHISEIDO

Ginza Tokyo

Urban Environment

Sun Dual Care

OIL-FREE

with HYALURONIC ACID

SPF 42

BROAD SPECTRUM SPF 42

WATER RESISTANT (40 MINUTES)

SUNSCREEN

50mL 1.6 FL. OZ.